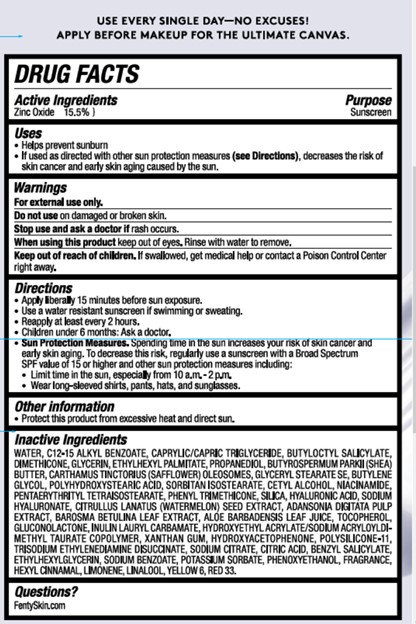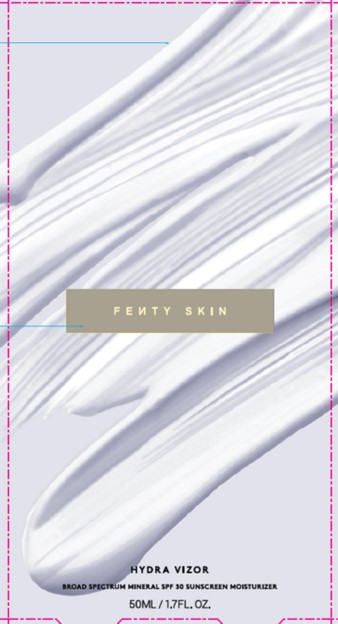 DRUG LABEL: FENTY SKIN HYDRA VIZOR BROAD SPECTRUM MINERAL SPF 30 SUNSCREEN MOISTURIZER
NDC: 71499-135 | Form: CREAM
Manufacturer: KENDO HOLDINGS INC
Category: otc | Type: HUMAN OTC DRUG LABEL
Date: 20250930

ACTIVE INGREDIENTS: ZINC OXIDE 15.5 g/100 mL
INACTIVE INGREDIENTS: SORBITAN ISOSTEARATE; CETYL ALCOHOL; PENTAERYTHRITYL TETRAISOSTEARATE; PHENYL TRIMETHICONE; SILICON DIOXIDE; WATERMELON SEED; ADANSONIA DIGITATA FRUIT PULP; AGATHOSMA BETULINA LEAF; ALOE VERA LEAF; GLUCONOLACTONE; INULIN LAURYL CARBAMATE; HYDROXYETHYL ACRYLATE/SODIUM ACRYLOYLDIMETHYL TAURATE COPOLYMER (100000 MPA.S AT 1.5%); XANTHAN GUM; D&C RED NO. 33; ETHYLHEXYLGLYCERIN; HYDROXYACETOPHENONE; DIMETHICONE/VINYL DIMETHICONE CROSSPOLYMER (SOFT PARTICLE); TRISODIUM ETHYLENEDIAMINE DISUCCINATE; CITRIC ACID MONOHYDRATE; LIMONENE, (+)-; LINALOOL, (+/-)-; BENZYL SALICYLATE; SODIUM CITRATE, UNSPECIFIED FORM; POTASSIUM SORBATE; .ALPHA.-HEXYLCINNAMALDEHYDE; SODIUM BENZOATE; FD&C YELLOW NO. 6; ALKYL (C12-15) BENZOATE; WATER; GLYCERIN; BUTYLOCTYL SALICYLATE; DIMETHICONE; MEDIUM-CHAIN TRIGLYCERIDES; SHEA BUTTER; NIACINAMIDE; HYALURONIC ACID; HYALURONATE SODIUM; PHENOXYETHANOL; ETHYLHEXYL PALMITATE; PROPANEDIOL; CARTHAMUS TINCTORIUS SEED OLEOSOMES; GLYCERYL STEARATE SE; BUTYLENE GLYCOL; TOCOPHEROL; POLYHYDROXYSTEARIC ACID (2300 MW)

KENDO - FENTY SKIN HYDRA VIZOR BROAD SPECTRUM MINERAL SPF 30 MOISTURIZER (71499-135)

ACTIVE INGREDIENTS

ZINC OXIDE 15.5%

PURPOSE

SUNSCREEN

USES

- HELPS PREVENT SUNBURN
- IF USED AS DIRECTED WITH OTHER SUN PROTECTION MEASURES (SEE DIRECTIONS), DECREASES THE RISK OF SKIN CANCER AND EARLY SKIN AGING CAUSED BY THE SUN.

WARNINGS

FOR EXTERNAL USE ONLY.

DO NOT USE ON DAMAGED OR BROKEN SKIN.

STOP USE AND ASK A DOCTOR IF RASH OCCURS.

WHEN USING THIS PRODUCT KEEP OUT OF EYES. RINSE WITH WATER TO REMOVE.

KEEP OUT OF REACH OF CHILDREN. IF SWALLOWED, GET MEDICAL HELP OR CONTACT A POISON CONTROL CENTER RIGHT AWAY.

DIRECTIONS

- APPLY LIBERALLY 15 MINUTES BEFORE SUN EXPOSURE.
- USE A WATER RESISTANT SUNSCREEN IF SWIMMING OR SWEATING.
- REAPPLY AT LEAST EVERY 2 HOURS.
- CHILDREN UNDER 6 MONTHS: ASK A DOCTOR.
- SUN PROTECTION MEASURES. SPENDING TIME IN THE SUN INCREASES YOUR RISK OF SKIN CANCER AND EARLY SKIN AGING. TO DECREASE THIS RISK, REGULARLY USE A SUNCREEN WITH A BROAD SPECTRUM SPF VALUE OF 15 OR HIGHER AND OTHER SUN PROTECTION MEASURES INCLUDING:
- LIMIT TIME IN THE SUN, ESPECIALLY FROM 10 A.M. - 2 P.M.
- WEAR LONG=SLEEVED SHIRTS, PANTS, HATS, AND SUNGLASSES.

OTHER INFORMATION

PROTECT THIS PRODUCT FROM EXCESSIVE HEAT AND DIRECT SUN.

INACTIVE INGREDIENTS

WATER, C12-15 ALKYL BENZOATE, CAPRYLIC/CAPRIC TRIGLYCERIDES, BUTYLOCTYL SALICYLATE, DIMETHICONE, GLYCERIN, ETHYLHEXYL PALMITATE, PROPANEDIOL, BUTYROSPREMUM PARKII (SHEA) BUTTER, CARTHAMUS TINCTORIUS (SAFFLOWER) .SEED OLEOSOMES, GLYCERYL STEARATE SE, BUTYLENE GLYCOL, POLYHYDROXYSTEARIC ACID, SORBITAN ISOSTEARATE, CETYL ALCOHOL, NIACINAMIDE, PENTAERYTHRITYL TETRAISOSTEARATE, PHENYL TRIMETHICONE, SILICA, HYALURONIC ACID, SODIUM HYALURONATE, CITRULLUS LANATUS (WATERMELON) SEED EXTRACT, ADANSONIA DIGITATA PULP EXTRACT, BAROSMA BETULINA LEAF EXTRACT, ALOE BARBADENSIS LEAF JUICE, TOCOPHEROL, GLUCONOLACTONE, INULIN LAURYL CARBAMATE, HYDROXYETHYL ACRYLATE/SODIUM ACRYLOYLDIMETHYL TAURATE COPOLYMER, XANTHAN GUM, HYDROXYACETOPHENONE, POLYSILICONE-11, TRISODIUM ETHYLENEDIAMINE DISUCCINATE, SODIUM CITRATE, CITRIC ACID, BENZYL SALICYLATE, ETHYLHEXYLGLYCERIN, SODIUM BENZOATE, POTASSIUM SORBATE, PHENOXYETHANOL, FRAGRANCE, HEXYL CINNAMAL, LIMONENE, LINALOOL, YELLOW 6, RED 33.

QUESTIONS?

FENTYSKIN.COM